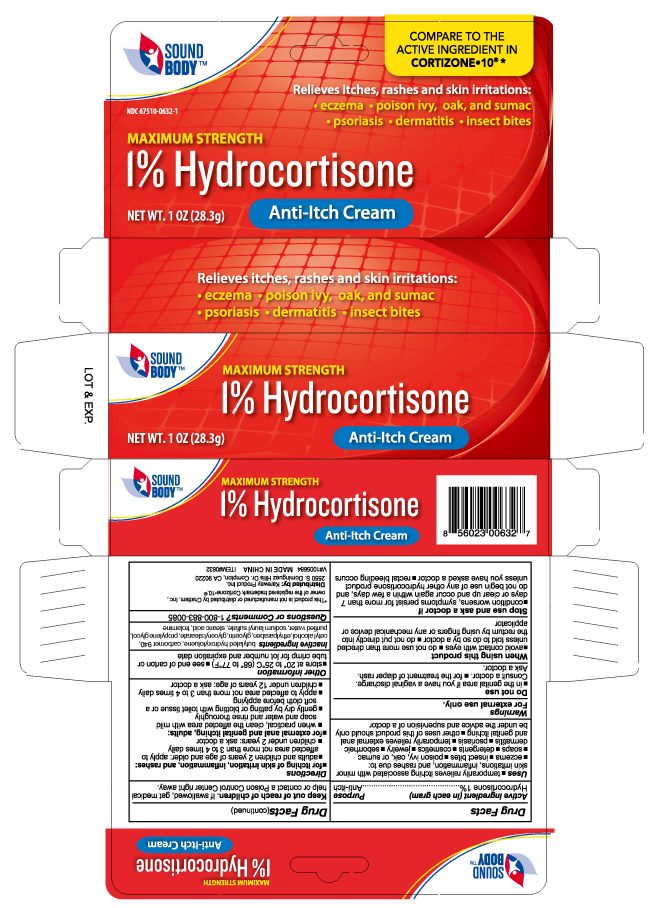 DRUG LABEL: Hydrocortisone
NDC: 67510-0632 | Form: CREAM
Manufacturer: Kareway Product, Inc.
Category: otc | Type: HUMAN OTC DRUG LABEL
Date: 20230127

ACTIVE INGREDIENTS: HYDROCORTISONE 1 g/100 g
INACTIVE INGREDIENTS: TROLAMINE; BUTYLATED HYDROXYTOLUENE; ETHYLPARABEN; CETYL ALCOHOL; GLYCERIN; CARBOMER 940; GLYCERYL 1-STEARATE; STEARIC ACID; PROPYLENE GLYCOL; SODIUM LAURYL SULFATE; WATER

Soundbody Hydrocortisone

Active Ingredient

Hydrocortisone 1%

Purpose

Anti-itch

Uses

temporarily relieves itching associated with minor sin irritation, inflammation and rashes due to:

- eczema
- insect bites
- poison ivy, oak, sumac
- soaps
- detergents
- cosmetics
- jewelry
- seborrheic dermatitis
- psoriasis
- temporarily relieves external anal and genital itching
- other uses of this product should only be under the advice and supervision of a doctor

Warnings

For external use only.

Do not use

- in the genital area if you have a vaginal discharge. Consult a doctor.
- for the treatment of diaper rash. Ask a doctor

When using this product

- avoid contact with eyes
- do not use more than directed unless told to do so by a doctor
- do not put directly into the rectum by using fingers or any mechanical device or applicator

Stop use and ask a doctor if

- condition worsens, symptoms persist for more than 7 days or clear up and occur again within a few days, and do not begin us of any other hydrocortisone product unless you have asked a doctor
- rectal bleeding occurs

Keep out of reach of children

If swallowed, get medical help or contact a Poison Control Center right away.

Directions

- for itching of skin irritation, inflammation, and rashes:
- adults and children 2 years of age and older: apply to affected area not more than 3 to 4 times daily
- children under 2 years: Ask a doctor
- for external anal and genital itching, adults:
- when practical, clean the affected area with mild soap and water and rinse thoroughly
- gently dry by patting or blotting with toilet tissue or a soft cloth before applying
- apply to affected area not more than 3 to 4 times daily
- children under 12 years of age: Ask a doctor

Other information

- store at 20 to 25oC (68 to 77oF)
- see end of carton or tube crimp for lot number and expiration date

INACTIVE INGREDIENT

butylated hydroxytoluene, carbomer 940, cetyl alcohol, ethylparaben, glycerin, glyceryl stearate, propylene glycol, sodium lauryl sulfate, stearic acid, trolamine, water

PACKAGE LABEL

Hydrocortisone